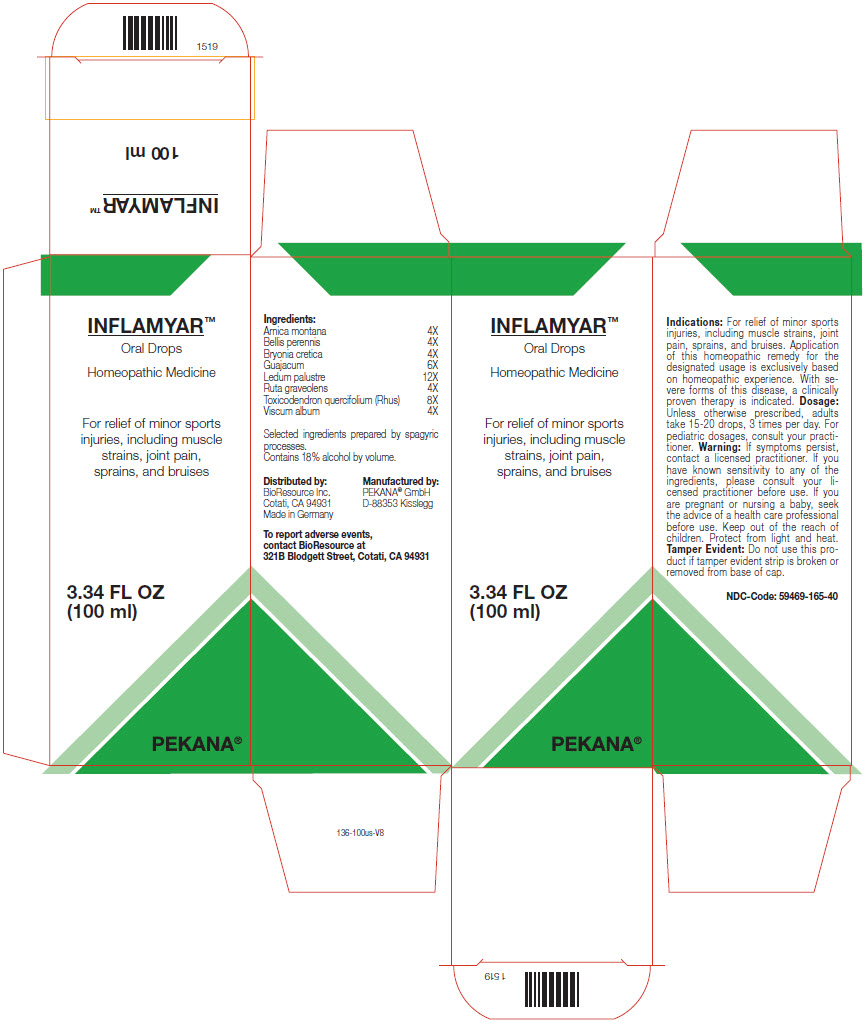 DRUG LABEL: INFLAMYAR
NDC: 59469-165 | Form: SOLUTION/ DROPS
Manufacturer: PEKANA Naturheilmittel GmbH
Category: homeopathic | Type: HUMAN OTC DRUG LABEL
Date: 20221215

ACTIVE INGREDIENTS: Arnica montana Root 4 [hp_X]/100 mL; BELLIS PERENNIS WHOLE 4 [hp_X]/100 mL; Bryonia Dioica Root 4 [hp_X]/100 mL; Guaiacum officinale Resin 6 [hp_X]/100 mL; RHODODENDRON TOMENTOSUM LEAFY TWIG 12 [hp_X]/100 mL; Ruta graveolens Flowering Top 4 [hp_X]/100 mL; Toxicodendron Pubescens Shoot 8 [hp_X]/100 mL; Viscum album Fruiting Top 4 [hp_X]/100 mL
INACTIVE INGREDIENTS: Water; Alcohol

INFLAMYAR™

ACTIVE INGREDIENT

Ingredients:
Arnica montana | 4X
Bellis perennis | 4X
Bryonia cretica | 4X
Guajacum | 6X
Ledum palustre | 12X
Ruta graveolens | 4X
Toxicodendron quercifolium (Rhus) | 8X
Viscum album | 4X

Selected ingredients prepared by spagyric processes.

INACTIVE INGREDIENT

Contains 18% alcohol by volume.

Indications

PURPOSE

For relief of minor sports injuries, including muscle strains, joint pain, sprains, and bruises. Application of this homeopathic remedy for the designated usage is exclusively based on homeopathic experience. With severe forms of this disease, a clinically proven therapy is indicated.

Dosage

Unless otherwise prescribed, adults take 10 pellets, 4 times per day. For pediatric dosages, consult your practitioner.

Warning

If symptoms persist, contact a licensed practitioner. If you have known sensitivity to any of the ingredients, please consult your licensed practitioner before use. If you are pregnant or nursing a baby, seek the advice of a health care professional before use.

Keep out of the reach of children.

STORAGE AND HANDLING

Protect from light and heat.

Tamper Evident

Do not use this product if tamper evident strip is broken or removed from base of cap.

QUESTIONS

To report adverse events, contact BioResource at 321B Blodgett Street, Cotati, CA 94931

Distributed by:
BioResource Inc.
Cotati, CA 94931

Manufactured by:
PEKANA® GmbH
D-88353 Kisslegg

PRINCIPAL DISPLAY PANEL - 100 ml Bottle Box

INFLAMYAR™

Oral Drops
Homeopathic Medicine

For relief of minor sports
injuries, including muscle
strains, joint pain,
sprains, and bruises

3.34 FL OZ
(100 ml)

PEKANA®